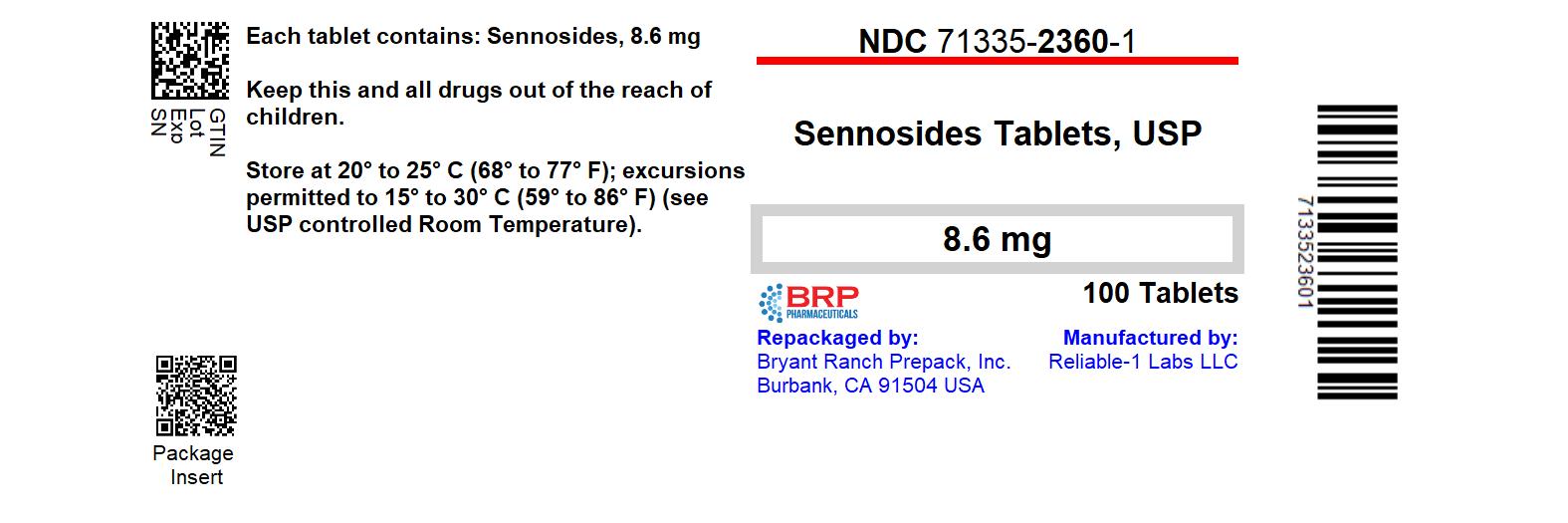 DRUG LABEL: Senna
NDC: 71335-2360 | Form: TABLET
Manufacturer: Bryant Ranch Prepack
Category: otc | Type: HUMAN OTC DRUG LABEL
Date: 20250626

ACTIVE INGREDIENTS: SENNOSIDES A AND B 8.6 mg/1 1
INACTIVE INGREDIENTS: CROSCARMELLOSE SODIUM; MICROCRYSTALLINE CELLULOSE; MAGNESIUM STEARATE; SILICON DIOXIDE

Senna 8.6mg

Drug Facts

Active ingredient (in each tablet)

Sennosides 8.6 mg

Purpose

Stimulant Laxative

Uses

- relieve occasional constipation (irregularity)
- this product generally produces a bowel movement in 6 to 12 hours

Warnings

Do not use

- Lasative products for longer than 1 week unless directed by a doctor

Ask a doctor before use if you have

- stomach pain
- nausea
- vomiting
- noticed a sudden change in bowel habits that continues over a period of 2 weeks

Stop use and ask a doctor if you have rectal bleeding or fail to have a bowel movement after use of a laxative. These may indicate a serious condition.

PREGNANCY OR BREAST FEEDING

If pregnant or breast-feeding, ask a health professional before use.

Keep out of reach of children. In case of overdose, get medical help or contact a Posion Control Center right away.

Other information

- each tablet contains: calcium 4 mg, sodium 3 mg
- store at 25°C (77°F); excursions permitted between 15°-30°C (59°-86°F)

Inactive ingredients

colloidal sillicon dioxide, croscarmellose sodium, magnesium stearate, microcrystalline cellulose

Questions or comments?

Call 516-341-0666

8:30am-4:30pm ET. Mon-Fri

Directions

take preferably at bedtime or as directed by a doctor

do not exceed maximum dosage

age | starting dosage | maximum dosage
adults and children 12 years of age or older | 2 tablets once a day | 4 tablets twice a day
children 6 to under 12 years | 1 tablet once a day | 2 tablets twice a day
children 2 to under 6 years | 1/2 tablet once a day | 1 tablet twice a day
children under 2 years | ask a doctor | ask a doctor

HOW SUPPLIED

Sennosides 8.6 mg: color brown (light), shape round, imprint code S5.

NDC: 71335-2360-1: 100 Tablets in a BOTTLE

NDC: 71335-2360-2: 60 Tablets in a BOTTLE

NDC: 71335-2360-3: 120 Tablets in a BOTTLE

NDC: 71335-2360-4: 56 Tablets in a BOTTLE

NDC: 71335-2360-5: 30 Tablets in a BOTTLE

NDC: 71335-2360-6: 90 Tablets in a BOTTLE

NDC: 71335-2360-7: 10 Tablets in a BOTTLE

Store at 25°C (77°F); excursions permitted between 15°-30°C (59°-86°F)

Repackaged/Relabeled by:
Bryant Ranch Prepack, Inc.
Burbank, CA 91504

PACKAGE LABEL

Sennosides 8.6mg Tablet